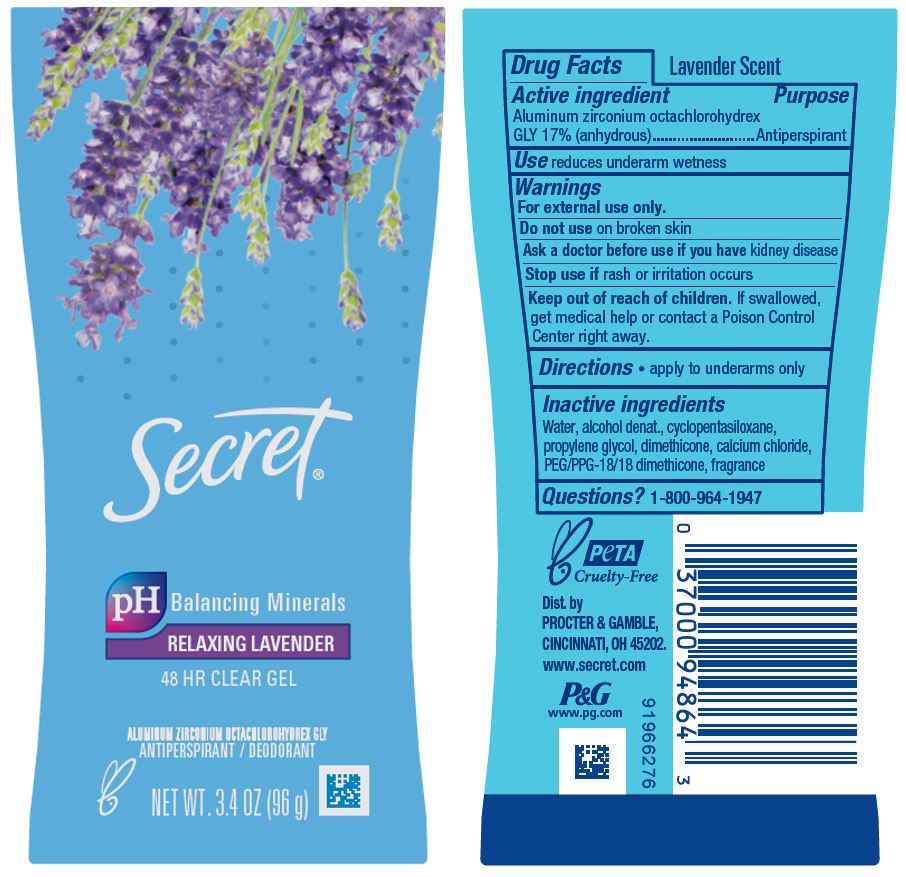 DRUG LABEL: Secret Relaxing Lavender Clear
NDC: 84126-005 | Form: GEL
Manufacturer: The Procter & Gamble Manufacturing Company
Category: otc | Type: HUMAN OTC DRUG LABEL
Date: 20250204

ACTIVE INGREDIENTS: ALUMINUM ZIRCONIUM OCTACHLOROHYDREX GLY 17 g/100 g
INACTIVE INGREDIENTS: PEG/PPG-18/18 DIMETHICONE; PROPYLENE GLYCOL; CALCIUM CHLORIDE; DIMETHICONE; CYCLOPENTASILOXANE; WATER; ALCOHOL

Secret Relaxing Lavender Invisible Solid

Drug Facts

Active ingredient

Aluminum zirconium octachlorohydrex Gly 17% (anhydrous)

Purpose

Antiperspirant

Use

reduces underarm wetness

Warnings

For external use only.

Do not use on broken skin

Ask a doctor before use if you have kidney disease

Stop use if rash or irritation occurs

Keep out of reach of children. If swallowed, get medical help or contact a Poison Control Center right away.

Directions

apply to underarms only

Inactive ingredients

Water, alcohol denat., cyclopentasiloxane, propylene glycol, dimethicone, calcium chloride, PEG/PPG-18/18 dimethicone, fragrance

Questions?

1-800-964-1947

www.secret.com

Dist. by PROCTER & GAMBLE,
CINCINNATI, OH 45202.

www.secret.com

PRINCIPAL DISPLAY PANEL - 96 g Canister Label

Secret®

pH Balancing Minerals

RELAXING LAVENDER

48 HR CLEAR GEL

ALUMINUM ZIRCONIUM OCTACHLOROHYDREX GLY

ANTIPERSPIRANT / DEODORANT

NET WT. 3.4 OZ